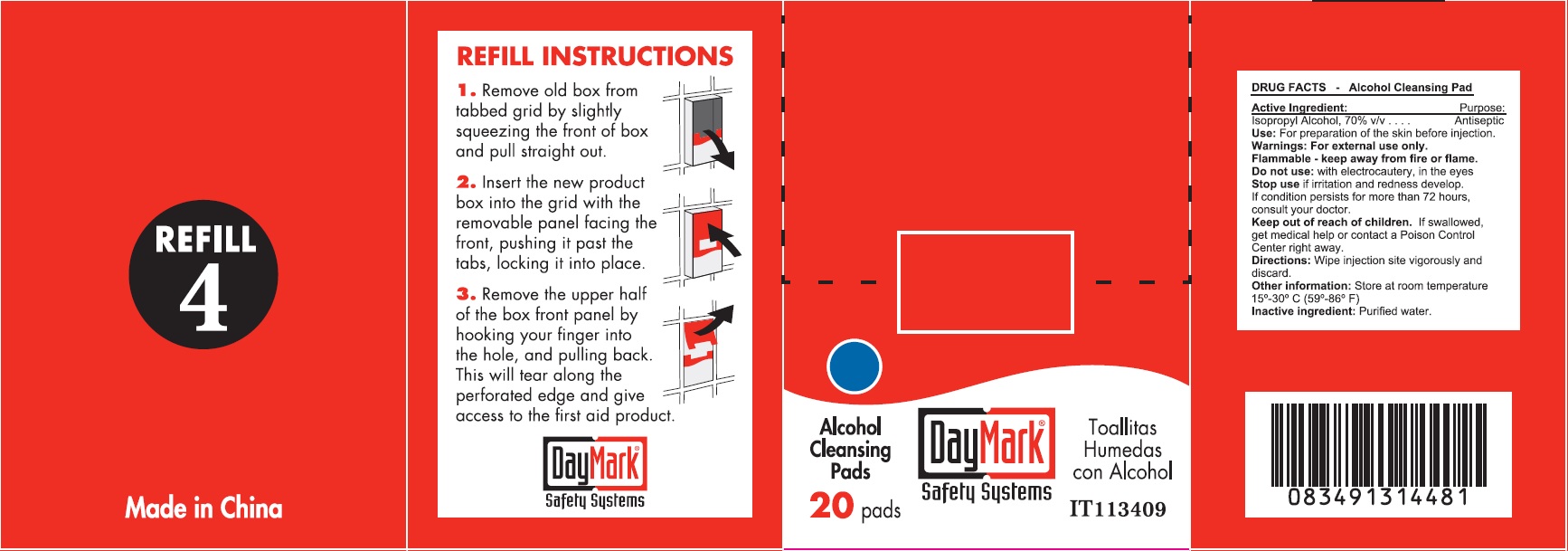 DRUG LABEL: Refill 4
NDC: 50814-018 | Form: CLOTH
Manufacturer: GFA Production (Xiamen) Co., Ltd.
Category: otc | Type: HUMAN OTC DRUG LABEL
Date: 20250127

ACTIVE INGREDIENTS: ISOPROPYL ALCOHOL 70 g/100 g
INACTIVE INGREDIENTS: WATER

Refill 4

Active Ingredient:

Isopropyl Alchol 70% v/v

Purpose:

Antiseptic

Use:

For preparation of the skin before injection.

Warnings

For external use only.

Flammable - keep away from fire or flame.

Do not use:

with electrocautery, in the eyes

Stop use

if irritation and redness develop, If condition persists for more than 72 hours, consult your doctor.

Keep out of reach of children.

If swallowed, get medical help or contact a Poison Control Center right away.

Directions:

Wipe injection site vigorously and discard.

Other information:

Store at room temperature 15°-30° C 59°-86° F)

Inactive ingredient:

Purified water.